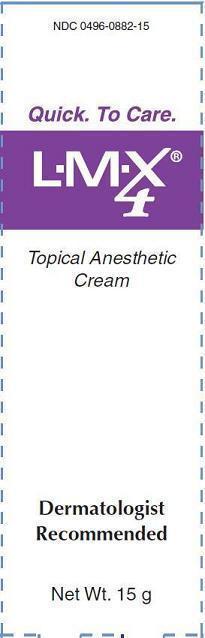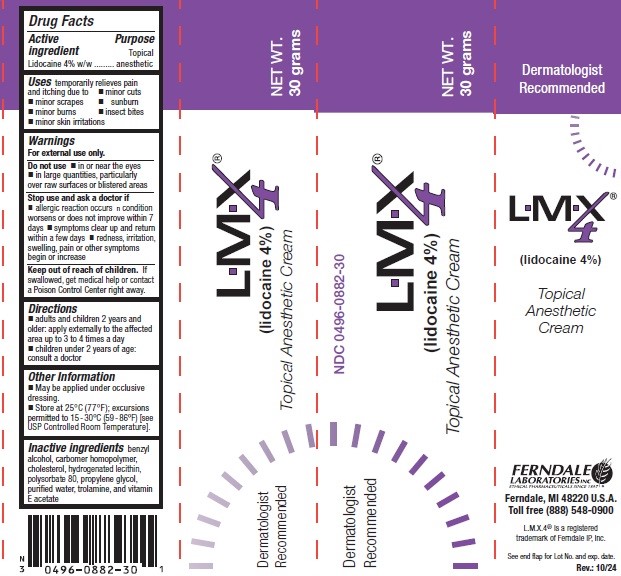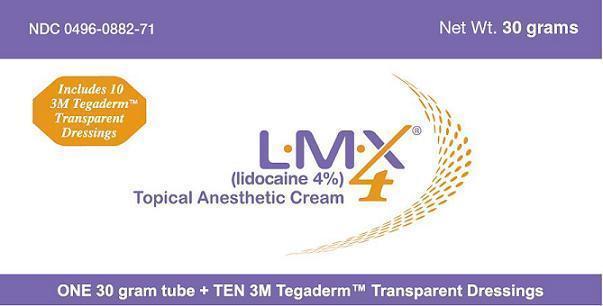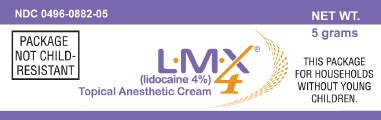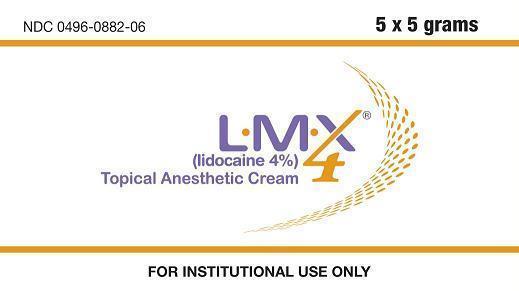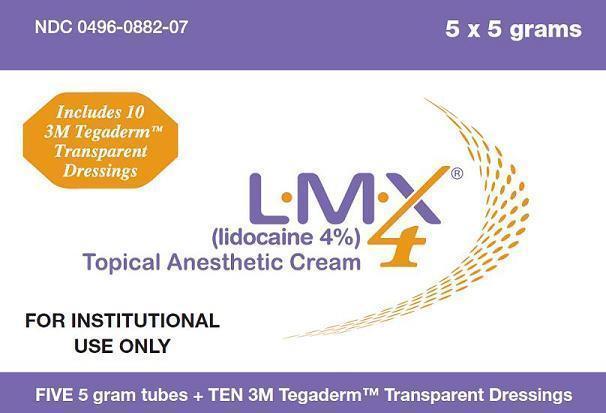 DRUG LABEL: LMX4
NDC: 0496-0882 | Form: CREAM
Manufacturer: Ferndale Laboratories, Inc.
Category: otc | Type: HUMAN OTC DRUG LABEL
Date: 20251210

ACTIVE INGREDIENTS: LIDOCAINE 40 mg/1 g
INACTIVE INGREDIENTS: BENZYL ALCOHOL; CARBOMER HOMOPOLYMER TYPE C; CHOLESTEROL; POLYSORBATE 80; PROPYLENE GLYCOL; TROLAMINE; ALPHA-TOCOPHEROL ACETATE; WATER

L.M.X.4

Active ingredient

Lidocaine 4% w/w

Purpose

Topical anesthetic

Uses

temporarily relieves pain and itching due to

- minor cuts
- minor scrapes
- minor burns
- sunburn
- minor skin irritations
- insect bites

Warnings

For external use only.

Do not use

- in or near the eyes
- in large quantities, particularly over raw surfaces or blistered areas

Stop use and ask a doctor if:

- allergic reaction occurs
- condition worsens or does not improve within 7 days
- symptoms clear up and return within a few days
- redness, irritation, swelling, pain or other symptoms begin or increase

Keep out of reach of children.

If swallowed, get medical help or contact a Poison Control Center right away.

Directions

- Adults and children 2 years and older: Apply externally to the affected area up to 3 to 4 times a day
- Children under 2 years: Consult a doctor

Other Information

- May be applied under occlusive dressing.
- Store at 25°C (77°F); excursions permitted to 15-30°C (59-86°F) [see USP Controlled Room Temperature].

Inactive ingredients

benzyl alcohol, carbomer homopolymer, cholesterol, hydrogenated lecithin, polysorbate 80, propylene glycol, purified water, trolamine, and vitamin E acetate

Package Labels-Principal Display Panels

Manufactured by Ferndale Laboratories, Inc.
Ferndale, MI 48220 U.S.A.
Toll free (888) 548-0900
www.ferndalelabs.com

L.M.X.4® is a registered trademark of Ferndale IP, Inc.
Tegaderm™ is a trademark of 3M Corporation.

NDC 0496-0882-06 L.M.X.4® 5 x 5 grams

NDC 0496-0882-07 L.M.X.4® 5 x 5 grams with 10 3M Tegaderm™ Transparent Dressings

NDC 0496-0882-15 L.M.X.4® 15 grams

NDC 0496-0882-30 L.M.X.4® 30 grams

NDC 0496-0882-71 L.M.X.4® 30 grams with 10 3M Tegaderm™ Transparent Dressings

NDC 0496-0882-05 L.M.X.4 5 grams